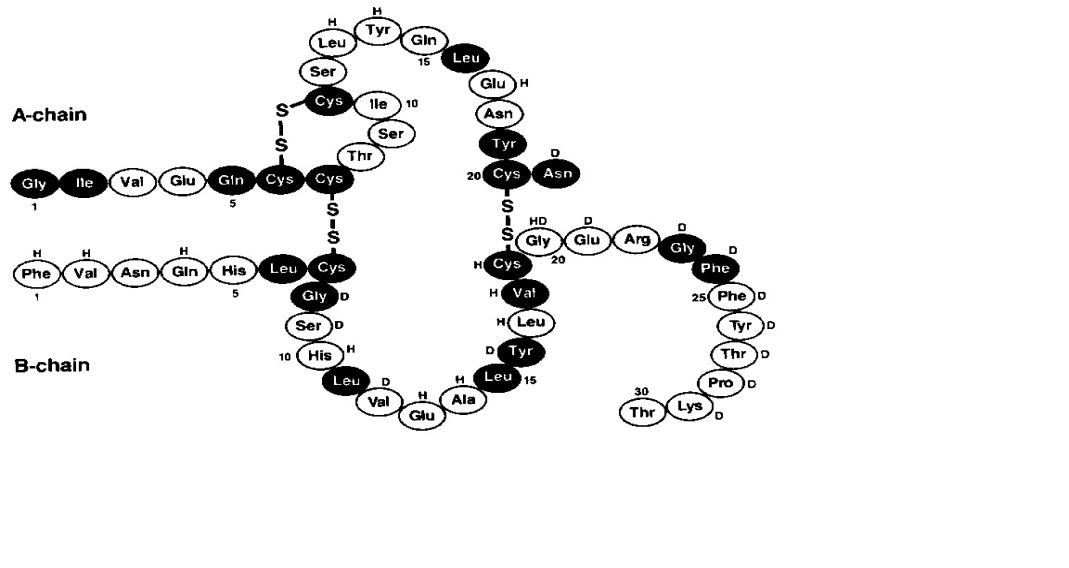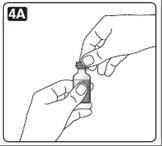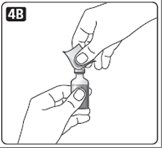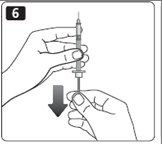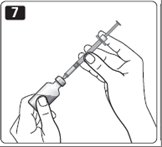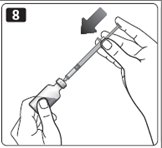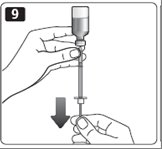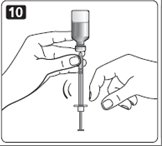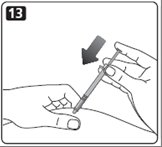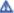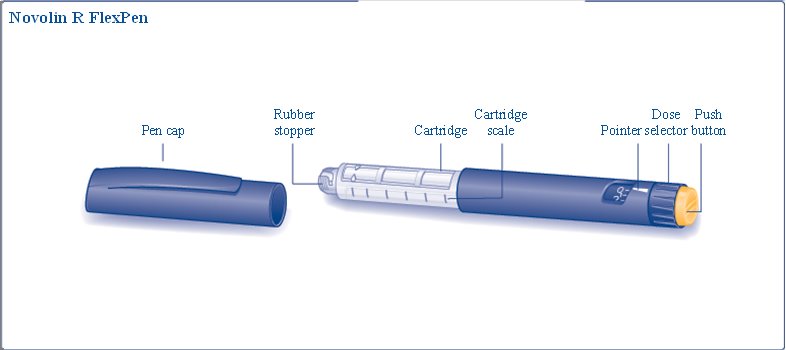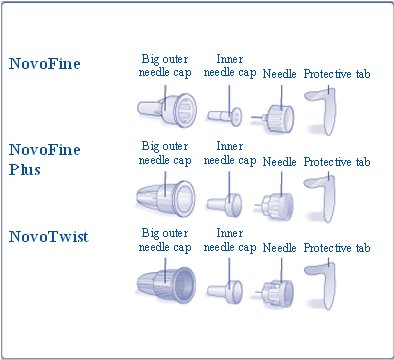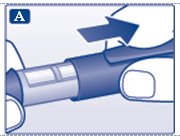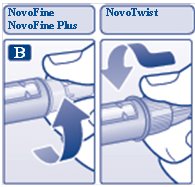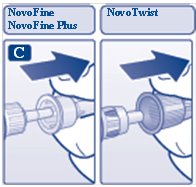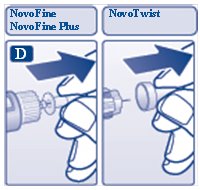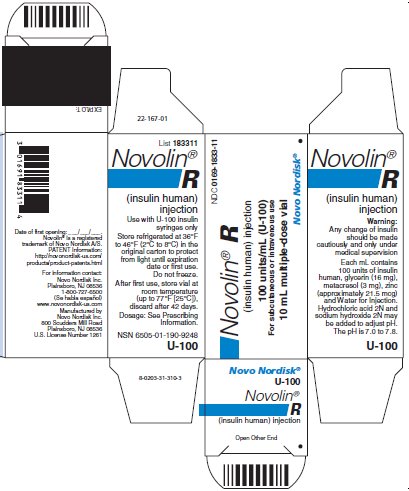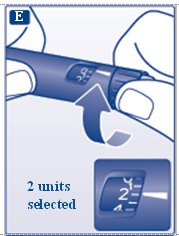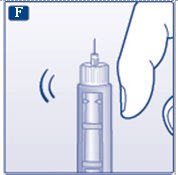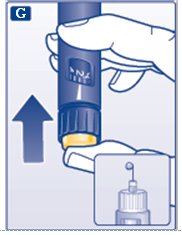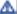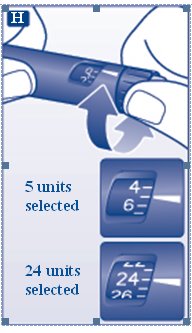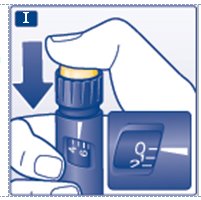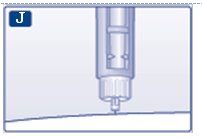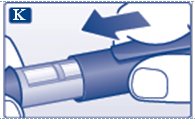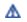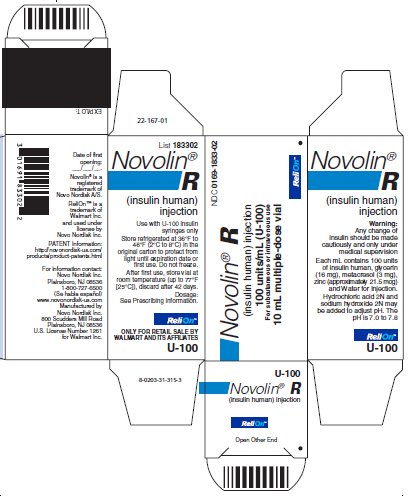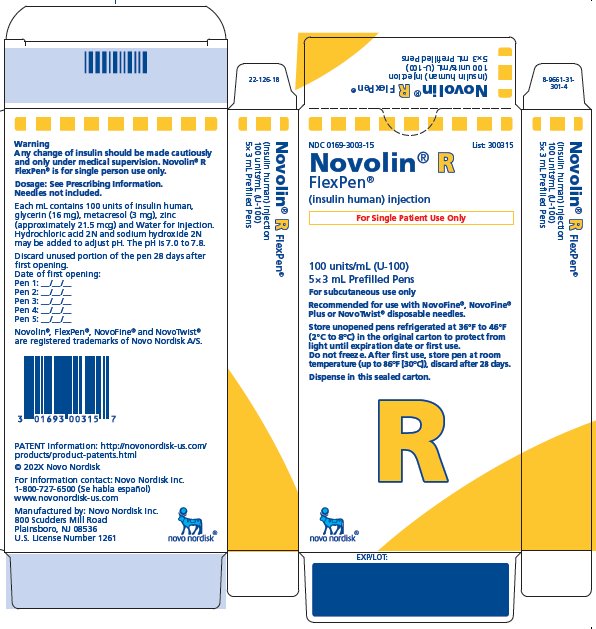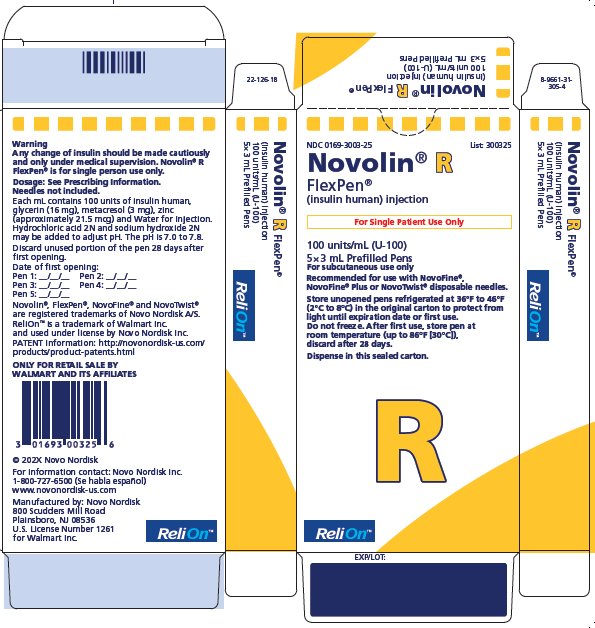 DRUG LABEL: Novolin
NDC: 0169-1833 | Form: INJECTION, SOLUTION
Manufacturer: Novo Nordisk
Category: otc | Type: HUMAN OTC DRUG LABEL
Date: 20221123

ACTIVE INGREDIENTS: INSULIN HUMAN 100 [iU]/1 mL
INACTIVE INGREDIENTS: ZINC 21 ug/1 mL; GLYCERIN 16 mg/1 mL; METACRESOL 3 mg/1 mL; HYDROCHLORIC ACID; SODIUM HYDROXIDE; WATER

HIGHLIGHTS OF PRESCRIBING INFORMATION

These highlights do not include all the information needed to use NOVOLIN R safely and effectively. See full prescribing information for NOVOLIN R.
NOVOLIN® R (insulin human) injection, for subcutaneous or intravenous use
Initial U.S. Approval: 1991

1 INDICATIONS AND USAGE

NOVOLIN R is a short-acting human insulin indicated to improve glycemic control in adults and pediatric patients with diabetes mellitus (1).

2 DOSAGE AND ADMINISTRATION

- See Full Prescribing Information for important administration instructions. (2.1)
- Subcutaneous injection: inject subcutaneously 30 minutes before a meal into the abdominal area, buttocks, thigh or the upper arm. Rotate injection sites to reduce risk of lipodystrophy and localized cutaneous amyloidosis. (2.2)
- Intravenous use: administer intravenously ONLY under medical supervision at concentrations from 0.05 unit/mL to 1 unit/mL in infusion systems using polypropylene infusion bags. (2.2)
- Individualize dose based on route of administration, metabolic needs, blood glucose monitoring results and glycemic control goal. (2.3)
- NOVOLIN R given by subcutaneous injection should generally be used in regimens with an intermediate- or long-acting insulin. (2.3)
- Can be mixed with NOVOLIN N. (2.5)

3 DOSAGE FORMS AND STRENGTHS

Injection: 100 units/mL (U-100) is available as:

- 10 mL multiple-dose vial (3)
- 3 mL single-patient-use NOVOLIN R FlexPen prefilled pen (3)

4 CONTRAINDICATIONS

- During episodes of hypoglycemia (4)
- Hypersensitivity to NOVOLIN R or any of its excipients (4)

5 WARNINGS AND PRECAUTIONS

- Never share a NOVOLIN R FlexPen or syringe between patients, even if the needle is changed. (5.1)
- Hyperglycemia or Hypoglycemia with Changes in Insulin Regimen: Make changes to a patient’s insulin regimen (e.g., insulin strength, manufacturer, type, injection site or method of administration) under close medical supervision with increased frequency of blood glucose monitoring. (5.2)
- Hypoglycemia: May be life-threatening. Increase frequency of blood glucose monitoring with changes to: insulin dosage, co-administered glucose lowering medications, meal pattern, physical activity; in patients with renal or hepatic impairment or with hypoglycemia unawareness. (5.3)
- Hypoglycemia Due to Medication Errors: Accidental mix-ups between insulin products can occur. Instruct patients to check insulin labels before injection. (5.4)
- Hypersensitivity Reactions: Severe, life-threatening, generalized allergy, including anaphylaxis, can occur. Discontinue NOVOLIN R, monitor, and treat if indicated. (5.5)
- Hypokalemia: May be life-threatening. Monitor potassium levels in patients at risk for hypokalemia and treat if indicated. (5.6)
- Fluid Retention and Heart Failure with Concomitant Use of Thiazolidinediones (TZDs): Observe for signs and symptoms of heart failure; consider dosage reduction or discontinuation if heart failure occurs. (5.7)

6 ADVERSE REACTIONS

Adverse reactions observed with NOVOLIN R include hypoglycemia, allergic reactions, injection site reactions, lipodystrophy, weight gain and edema (6).

To report SUSPECTED ADVERSE REACTIONS, contact Novo Nordisk Inc. at 1-800-727-6500 or FDA at 1-800-FDA-1088 or www.fda.gov/medwatch.

7 DRUG INTERACTIONS

- Drugs that Affect Glucose Metabolism: Adjustment of insulin dosage may be needed. (7)
- Antiadrenergic Drugs (e.g., beta-blockers, clonidine, guanethidine, and reserpine): Signs and symptoms of hypoglycemia may be reduced or absent. (5.3, 7)

FULL PRESCRIBING INFORMATION

1 INDICATIONS AND USAGE

NOVOLIN R is indicated to improve glycemic control in adults and pediatric patients with diabetes mellitus.

2 DOSAGE AND ADMINISTRATION

2.1 Important Administration Instructions

Always check insulin labels before administration [see Warnings and Precautions (5.4)].

- Inspect NOVOLIN R visually before use. It should appear clear and colorless. Do not use NOVOLIN R if particulate matter or coloration is seen.
- Use of NOVOLIN R in insulin pumps is not recommended because of the risk of precipitation.

2.2 Route of Administration

Subcutaneous Administration

- Inject NOVOLIN R subcutaneously approximately 30 minutes prior to the start of a meal into the abdominal area, buttocks, thigh, or the upper arm.
- Rotate injection sites within the same region from one injection to the next to reduce the risk of lipodystrophy and localized cutaneous amyloidosis. Do not inject into areas of lipodystrophy or localized cutaneous amyloidosis [see Warnings and Precautions (5.2), Adverse Reactions (6)].

Intravenous Administration

- Administer NOVOLIN R intravenously ONLY under medical supervision with close monitoring of blood glucose and potassium levels to reduce the risk of hypoglycemia and hypokalemia [see Warnings and Precautions (5.3, 5.6) and How Supplied/Storage and Handling (16.2)].
- Dilute NOVOLIN R to concentrations from 0.05 unit/mL to 1 unit/mL insulin in infusion systems using polypropylene infusion bags. NOVOLIN R is stable in infusion fluids such as 0.9% sodium chloride, 5% dextrose, or 10% dextrose with 40 mmol/L potassium chloride. Intravenous infusion bags are stable at room temperature for 24 hours.

2.3 Dosage Information

- Individualize and adjust the dosage of NOVOLIN R based on route of administration, the individual's metabolic needs, blood glucose monitoring results and glycemic control goal.
- NOVOLIN R given by subcutaneous injection should generally be used in regimens that include an intermediate or long-acting insulin.
- During changes to a patient’s insulin regimen, increase the frequency of blood glucose monitoring [see Warnings and Precautions (5.2)].
- Dosage adjustments may be needed with changes in physical activity, changes in meal patterns (i.e., macronutrient content or timing of food intake), changes in renal or hepatic function or during acute illness [see Warnings and Precautions (5.2, 5.3) and Use in Specific Populations (8.6,8.7)].
- Dosage adjustment may be needed when switching from another insulin to NOVOLIN R [see Warnings and Precautions (5.2)].

2.4 Dosage Adjustment due to Drug Interactions

- Dosage adjustment may be needed when NOVOLIN R is co-administered with certain drugs [see Drug Interactions (7)].

2.5 Instructions for Mixing with Other Insulins for Subcutaneous Injection

- NOVOLIN R can be mixed with NOVOLIN N.
- When mixing, the NOVOLIN R should be drawn into the syringe first and the mixture should be injected immediately after mixing.

3 DOSAGE FORMS AND STRENGTHS

Injection: 100 units/mL (U-100), a clear and colorless solution available as:

- 10 mL multiple-dose vial
- 3 mL single-patient-use NOVOLIN R FlexPen prefilled pen

4 CONTRAINDICATIONS

NOVOLIN R is contraindicated:

- During episodes of hypoglycemia
- In patients with hypersensitivity to NOVOLIN R or any of its excipients

5 WARNINGS AND PRECAUTIONS

5.1 Never Share a NOVOLIN R FlexPen or Syringe between Patients

NOVOLIN R FlexPen must never be shared between patients, even if the needle is changed. Patients using NOVOLIN R vials must never share needles or syringes with another person. Sharing poses a risk for transmission of blood-borne pathogens.

5.2 Hyperglycemia or Hypoglycemia with Changes in Insulin Regimen

Changes in an insulin regimen (e.g., insulin strength, manufacturer, type, injection site or method of administration) may affect glycemic control and predispose to hypoglycemia [see Warnings and Precautions (5.3)] or hyperglycemia. Repeated insulin injections into areas of lipodystrophy or localized cutaneous amyloidosis have been reported to result in hyperglycemia; and a sudden change in the injection site (to an unaffected area) has been reported to result in hypoglycemia [see Adverse Reactions (6)].

Make any changes to a patient’s insulin regimen under close medical supervision with increased frequency of blood glucose monitoring. Advise patients who have repeatedly injected into areas of lipodystrophy or localized cutaneous amyloidosis to change the injection site to unaffected areas and closely monitor for hypoglycemia. For patients with type 2 diabetes, dosage adjustments of concomitant anti-diabetic products may be needed.

5.3 Hypoglycemia

Hypoglycemia is the most common adverse reaction of all insulins, including NOVOLIN R. Severe hypoglycemia can cause seizures, may lead to unconsciousness, may be life threatening or cause death. Hypoglycemia can impair concentration ability and reaction time; this may place the patient and others at risk in situations where these abilities are important (e.g., driving or operating other machinery).

Hypoglycemia can happen suddenly and symptoms may differ in each patient and change over time in the same patient. Symptomatic awareness of hypoglycemia may be less pronounced in patients with longstanding diabetes in patients with diabetic neuropathy, in patients using medications that block the sympathetic nervous system (e.g., beta-blockers) [see Drug Interactions (7)], or in patients who experience recurrent hypoglycemia.

Risk Factors for Hypoglycemia

The risk of hypoglycemia after an injection is related to the duration of action of the insulin and, in general, is highest when the glucose lowering effect of the insulin is maximal. As with all insulins, the glucose lowering effect time course of NOVOLIN R may vary in different individuals or at different times in the same individual and depends on many conditions, including the area of injection as well as the injection site blood supply and temperature [see Clinical Pharmacology (12.2)]. Other factors which may increase the risk of hypoglycemia include changes in meal pattern (e.g., macronutrient content or timing of meals), changes in level of physical activity, or changes to concomitant drugs [see Drug Interactions (7)]. Patients with renal or hepatic impairment may be at higher risk of hypoglycemia [see Use in Specific Populations (8.6, 8.7)].

Risk Mitigation Strategies for Hypoglycemia

Patients and caregivers must be educated to recognize and manage hypoglycemia. Self-monitoring of blood glucose plays an essential role in the prevention and management of hypoglycemia. In patients at higher risk for hypoglycemia and patients who have reduced symptomatic awareness of hypoglycemia, increased frequency of blood glucose monitoring is recommended.

5.4 Hypoglycemia Due to Medication Errors

Accidental mix-ups between NOVOLIN R and other insulin products have been reported. To avoid medication errors between NOVOLIN R and other insulins, instruct patients to always check the insulin label before each injection.

5.5 Hypersensitivity Reactions

Severe, life-threatening, generalized allergy, including anaphylaxis, can occur with NOVOLIN R. Generalized allergy to insulin may manifest as a whole body rash (including pruritus), dyspnea, wheezing, hypotension, tachycardia, or diaphoresis. If hypersensitivity reactions occur, discontinue NOVOLIN R; treat per standard of care and monitor until symptoms and signs resolve. NOVOLIN R is contraindicated in patients who have had hypersensitivity reactions to insulin human injection or its excipients.

5.6 Hypokalemia

All insulins, including NOVOLIN R, cause a shift in potassium from the extracellular to intracellular space, possibly leading to hypokalemia. Untreated hypokalemia may cause respiratory paralysis, ventricular arrhythmia, and death. Monitor potassium levels in patients at risk for hypokalemia if indicated (e.g., patients using potassium-lowering medications, patients taking medications sensitive to serum potassium concentration).

5.7 Fluid Retention and Heart Failure with Concomitant Use of PPAR-gamma agonists

Thiazolidinediones (TZDs), which are peroxisome proliferator-activated receptor (PPAR)-gamma agonists, can cause dose-related fluid retention when used in combination with insulin. Fluid retention may lead to or exacerbate heart failure. Patients treated with insulin, including NOVOLIN R, and a PPAR-gamma agonist should be observed for signs and symptoms of heart failure. If heart failure develops, it should be managed according to current standards of care, and discontinuation or dose reduction of the PPAR-gamma agonist must be considered.

6 ADVERSE REACTIONS

The following adverse reactions are also discussed elsewhere in the labeling:

- Hypoglycemia [see Warnings and Precautions (5.3)]
- Medication Errors [see Warnings and Precautions (5.4)]
- Hypersensitivity Reactions [see Warnings and Precautions (5.5)]
- Hypokalemia [see Warnings and Precautions (5.6)]

Adverse Reactions from Clinical Studies or Postmarketing Reports

The following additional adverse reactions have been identified during clinical studies or from postmarketing reports with use of NOVOLIN R. Because some of these reactions are reported voluntarily from a population of uncertain size, it is not always possible to reliably estimate their frequency or to establish a causal relationship to drug exposure.

Adverse reactions associated with insulin initiation and glucose control intensification

Intensification or rapid improvement in glucose control has been associated with a transitory, reversible ophthalmologic refraction disorder, worsening of diabetic retinopathy, and acute painful peripheral neuropathy. Over the long-term, improved glycemic control decreases the risk of diabetic retinopathy and neuropathy.

Hypersensitivity reactions

Severe, life-threatening, generalized allergy, including anaphylaxis.

Hypoglycemia

Hypoglycemia is the most commonly observed adverse reaction in NOVOLIN R.

Hypokalemia

NOVOLIN R can cause a shift in potassium from the extracellular to intracellular space, possibly leading to hypokalemia.

Injection site reactions

NOVOLIN R can cause local injection site reactions including redness, swelling, or itching at the site of injection. These reactions usually resolve in a few days to a few weeks, but in some occasions, may require discontinuation. Localized reactions and generalized myalgias have been reported with the use of metacresol, which is an excipient in NOVOLIN R.

Lipodystrophy

Administration of insulin subcutaneously, including NOVOLIN R, has resulted in lipoatrophy (depression in the skin) or lipohypertrophy (enlargement or thickening of tissue) [see Dosage and Administration (2.2)] in some patients.

Localized Cutaneous Amyloidosis

Localized cutaneous amyloidosis at the injection site has occurred. Hyperglycemia has been reported with repeated insulin injections into areas of localized cutaneous amyloidosis; hypoglycemia has been reported with a sudden change to an unaffected injection site.

Medication Errors

Medication errors in which other insulins have been accidentally substituted for NOVOLIN R have been identified during postapproval use.

Peripheral edema

Insulins, including NOVOLIN R, may cause sodium retention and edema, particularly if previously poor metabolic control is improved by intensified insulin therapy.

Weight gain

Weight gain can occur with insulins, including NOVOLIN R, and has been attributed to the anabolic effects of insulin and the decrease in glucosuria.

Immunogenicity

As with all therapeutic proteins, insulin administration may cause anti-insulin antibodies to form. Increases in titers of anti-insulin antibodies that react with human insulin have been observed in patients treated with NOVOLIN R.

7 DRUG INTERACTIONS

Table 1: Clinically Significant Drug Interactions with NOVOLIN R

Drugs that May Increase the Risk of Hypoglycemia
Drugs: | Antidiabetic agents, ACE inhibitors, angiotensin II receptor blocking agents, disopyramide, fibrates, fluoxetine, monoamine oxidase inhibitors, pentoxifylline, pramlintide, salicylates, somatostatin analog (e.g., octreotide), and sulfonamide antibiotics
Intervention: | Dose adjustment and increased frequency of glucose monitoring may be required when NOVOLIN R is co-administered with these drugs.
Drugs that May Decrease the Blood Glucose Lowering Effect of NOVOLIN R
Drugs: | Atypical antipsychotics (e.g., olanzapine and clozapine), corticosteroids, danazol, diuretics, estrogens, glucagon, isoniazid, niacin, oral contraceptives, phenothiazines, progestogens (e.g., in oral contraceptives), protease inhibitors, somatropin, sympathomimetic agents (e.g., albuterol, epinephrine, terbutaline), and thyroid hormones.
Intervention: | Dose adjustment and increased frequency of glucose monitoring may be required when NOVOLIN R is co-administered with these drugs.
Drugs that May Increase or Decrease the Blood Glucose Lowering Effect of NOVOLIN R
Drugs: | Alcohol, beta-blockers, clonidine, and lithium salts. Pentamidine may cause hypoglycemia, which may sometimes be followed by hyperglycemia.
Intervention: | Dose adjustment and increased frequency of glucose monitoring may be required when NOVOLIN R is co-administered with these drugs.
Drugs that May Blunt Signs and Symptoms of Hypoglycemia
Drugs: | Beta-blockers, clonidine, guanethidine, and reserpine
Intervention: | Increased frequency of glucose monitoring may be required when NOVOLIN R is co-administered with these drugs.

8 USE IN SPECIFIC POPULATIONS

8.1 Pregnancy

Risk Summary

Available data from published studies over decades have not established an association with human insulin use during pregnancy and major birth defects, miscarriage or adverse maternal or fetal outcomes (see Data). There are risks to the mother and fetus associated with poorly controlled diabetes in pregnancy (see Clinical Considerations). Animal reproduction studies were not performed.

The estimated background risk of major birth defects is 6-10% in women with pre-gestational diabetes with a HbA1c >7 and has been reported to be as high as 20-25% in women with a HbA1c >10. The estimated background risk of miscarriage for the indicated population is unknown. In the U.S. general population, the estimated background risk of major birth defects and miscarriage in clinically recognized pregnancies is 2-4% and 15-20%, respectively.

Clinical Considerations

Disease-associated maternal and/or embryo/fetal risk

Poorly controlled diabetes in pregnancy increases the maternal risk for diabetic ketoacidosis, pre-eclampsia, spontaneous abortions, preterm delivery, and delivery complications. Poorly controlled diabetes increases the fetal risk for major birth defects, stillbirth, and macrosomia-related morbidity.

Data

Human Data

While available studies cannot definitively establish the absence of risk, published data from retrospective studies, open-label, randomized, parallel studies and meta-analyses have not established an association with human insulin use during pregnancy and major birth defects, miscarriage, or adverse maternal or fetal outcomes. All available studies have methodological limitations including lack of blinding, unclear methods of randomization, and small sample size.

8.2 Lactation

Risk Summary

Available data from published literature suggest that exogenous human insulin products, including NOVOLIN R, are transferred into human milk. There are no adverse reactions reported in the breastfed infants in the literature. There are no data on the effects of exogenous human insulin products, including NOVOLIN R, on milk production. The developmental and health benefits of breastfeeding should be considered along with the mother’s clinical need for NOVOLIN R and any potential adverse effects on the breastfed infant from NOVOLIN R or from the underlying maternal condition.

8.4 Pediatric Use

NOVOLIN R is indicated to improve glycemic control in pediatric patients with diabetes mellitus.

The dosage of NOVOLIN R must be individualized in pediatric patients based on metabolic needs and frequent monitoring of blood glucose to reduce the risk of hypoglycemia [see Dosage and Administration (2.3) and Warnings and Precautions (5.3)].

8.5 Geriatric Use

In clinical trials 18 of 1285 patients (1.4%) with type 1 diabetes and 151 of 635 patients (24%) with type 2 diabetes treated with NOVOLIN R were ≥65 years of age. Therefore, conclusions are limited regarding the efficacy and safety of NOVOLIN R in patients ≥65 years of age. The effect of age on the pharmacokinetics and pharmacodynamics of NOVOLIN R has not been studied.

Elderly patients using NOVOLIN R, may be at increased risk of hypoglycemia due to co-morbid disease [see Warnings and Precautions (5.3)].

8.6 Renal Impairment

The effect of renal impairment on the pharmacokinetics and pharmacodynamics of NOVOLIN R has not been studied. Patients with renal impairment are at increased risk of hypoglycemia and may require more frequent NOVOLIN R dose adjustment and more frequent blood glucose monitoring [see Warnings and Precautions (5.3)].

8.7 Hepatic Impairment

The effect of hepatic impairment on the pharmacokinetics and pharmacodynamics of NOVOLIN R has not been studied. Patients with hepatic impairment are at increased risk of hypoglycemia and may require more frequent NOVOLIN R dose adjustment and more frequent blood glucose monitoring [see Warnings and Precautions (5.3)].

10 OVERDOSAGE

Excess insulin administration may cause hypoglycemia and, particularly when given intravenously, hypokalemia. Mild episodes of hypoglycemia usually can be treated with oral glucose. Adjustments in drug dosage, meal patterns, or exercise may be needed. More severe episodes with coma, seizure, or neurologic impairment can be treated with intramuscular or subcutaneous glucagon or intravenous glucose. Sustained carbohydrate intake and observation may be necessary because hypoglycemia may recur after apparent clinical recovery. Hypokalemia must be corrected appropriately [see Warnings and Precautions (5.3, 5.6)].

11 DESCRIPTION

Insulin human is a short-acting human insulin produced by recombinant DNA technology, utilizing Saccharomyces cerevisiae (baker’s yeast) as the production organism and has the empirical formula C257H383N65O77S6 with a molecular weight of 5808 Da.

Figure 1: Structural formula of NOVOLIN R

NOVOLIN R (insulin human) injection is a sterile, clear and colorless solution for subcutaneous or intravenous use. Each mililiter of NOVOLIN R contains 100 units of insulin human, and glycerin (16 mg), metacresol (3 mg), zinc (approximately 21 mcg/mL) and Water for Injection. Hydrochloric acid 2N and sodium hydroxide 2N may be added during manufacture to adjust pH. The pH is 7.0 to 7.8.

12 CLINICAL PHARMACOLOGY

12.1 Mechanism of Action

The primary activity of insulin, including NOVOLIN R is the regulation of glucose metabolism. Insulins lower blood glucose by stimulating peripheral glucose uptake, especially by skeletal muscle and fat, and by inhibiting hepatic glucose production. Insulin inhibits lipolysis and proteolysis, and enhances protein synthesis.

12.2 Pharmacodynamics

NOVOLIN R is a short-acting insulin. The time course of insulin action (i.e., glucose lowering) may vary considerably in different individuals, within the same individual, and different doses. When injected subcutaneously, the glucose-lowering effect of NOVOLIN R begins approximately 30 minutes post-dose, is maximal between 1.5 and 3.5 hours post-dose and terminates approximately 8 hours post-dose. The onset of action of NOVOLIN R, when administered intravenously, is more rapid in comparison to the subcutaneous administration. When injected subcutaneously, NOVOLIN R has a slower onset of action and longer duration of action compared to the rapid-acting insulin analogs.

12.3 Pharmacokinetics

After single subcutaneous administration of 0.1 unit/kg of NOVOLIN R to healthy subjects, peak insulin concentrations occurred between 1.5 to 2.5 hours post-dose. On average, insulin concentrations returned to baseline at around 5 hours post-dose.

The effects of gender, age, obesity, renal and hepatic impairment on the pharmacodynamics and pharmacokinetics of NOVOLIN R have not been studied.

13 NONCLINICAL TOXICOLOGY

13.1 Carcinogenesis, Mutagenesis, Impairment of Fertility

Standard 2-year carcinogenicity studies in animals have not been performed to evaluate the carcinogenic potential of NOVOLIN R.

NOVOLIN R is not mutagenic in the following in vitro tests: The chromosomal aberration assay in human lymphocytes, the micronucleus assay in mouse polychromatic erythrocytes, and the mutation frequency assay in Chinese hamster cells.

Standard reproduction and teratology studies in animals, including fertility assessments have not been conducted with NOVOLIN R.

16 HOW SUPPLIED/STORAGE AND HANDLING

16.1 How Supplied

NOVOLIN R (insulin human) injection is 100 units/mL (U-100), a clear and colorless solution available as:

10 mL multiple-dose vial |  | NDC 0169-1833-11
10 mL multiple-dose vial | ReliOn® brand | NDC 0169-1833-02
3 mL single-patient-use FlexPen |  | NDC 0169-3003-15
3 mL single-patient-use FlexPen | ReliOn® brand | NDC 0169-3003-25

The NOVOLIN R FlexPen dials in 1-unit increments.

16.2 Storage and Handling

Dispense in the original sealed carton with the enclosed Instructions for Use.
2. Do not freeze.
3. Do not use if it has been frozen.
4. Do not use after the expiration date.
5. Do not expose to excessive heat or light.

NOVOLIN R FlexPen must never be shared between patients, even if the needle is changed. Always remove and discard the needle after each injection from the NOVOLIN R FlexPen and store without a needle attached.

Patients using NOVOLIN R vials must never share needles or syringes with another person. Always use a new disposable syringe or needle for each injection to prevent contamination.

Table 2: Storage Conditions and Expiration Dates for NOVOLIN R

 | Not In-use; (Unopened); Refrigerated; (36°F - 46°F; [2°C - 8°C]) | Not In-use; (Unopened); Room Temperature; (see temperature below) | In-use; (Opened); Room Temperature; (see temperature below)
10 mL multiple-dose vial | Until expiration date | 42 days; up to 77°F (25°C) | 42 days; up to 77°F (25°C); (Do not refrigerate)
3 mL single-patient-use FlexPen | Until expiration date | 28 days; up to 86°F (30°C) | 28 days; up to 86°F (30°C); (Do not refrigerate)

Intravenous infusion bags prepared as indicated [see Dosage and Administration (2.2)] are stable at room temperature for 24 hours.

17 PATIENT COUNSELING INFORMATION

Advise the patient to read the FDA-approved patient labeling (Patient Information and Instructions for Use).

Never Share a NOVOLIN R FlexPen or Syringe between Patients

Advise patients using NOVOLIN R vials or FlexPen not to share needles, syringes or FlexPen with another person. Sharing poses a risk for transmission of blood-borne pathogens [see Warnings and Precautions (5.1)].

Hyperglycemia or Hypoglycemia

Inform patients that hypoglycemia is the most common adverse reaction with insulin. Instruct patients on self-management procedures including glucose monitoring, proper injection technique, and management of hypoglycemia and hyperglycemia, especially at initiation of NOVOLIN R therapy. Instruct patients on handling of special situations such as intercurrent conditions (illness, stress, or emotional disturbances), an inadequate or skipped insulin dose, inadvertent administration of an increased insulin dose, inadequate food intake, and skipped meals. Instruct patients on the management of hypoglycemia [see Warnings and Precautions (5.3)].

Inform patients that their ability to concentrate and react may be impaired as a result of hypoglycemia. Advise patients who have frequent hypoglycemia or reduced or absent warning signs of hypoglycemia to use caution when driving or operating machinery.

Advise patients that changes in insulin regimen can predispose to hyperglycemia or hypoglycemia and that changes in insulin regimen should be made under close medical supervision [see Warnings and Precautions (5.2).

Hypoglycemia due to Medication Errors

Instruct patients to always check the insulin label before each injection to avoid mix-ups between insulin products [see Warnings and Precautions (5.4)].

Hypersensitivity Reactions

Advise patients that hypersensitivity reactions have occurred with NOVOLIN R. Inform patients on the symptoms of hypersensitivity reactions and to seek medical attention if they occur [see Warnings and Precautions (5.5)].

Novolin®, FlexPen® and Novo Nordisk® are registered trademarks of Novo Nordisk A/S.

ReliOn® is a registered trademark of Walmart Inc. and is used under license by Novo Nordisk Inc.

Patent Information: http://novonordisk-us.com/products/product-patents.html

© 2022 Novo Nordisk

Manufactured by:

Novo Nordisk Inc.

800 Scudders Mill Road

Plainsboro, New Jersey 08536

1-800-727-6500

U.S. License Number 1261

For information about NOVOLIN R contact:

Novo Nordisk Inc.

800 Scudders Mill Road

Plainsboro, New Jersey 08536

www.novonordisk-us.com

1-800-727-6500 (Se habla español)

Patient Package Insert

Patient Information

NOVOLIN® R (NO-voe-lin)

(insulin human) injection for subcutaneous or intravenous use

Do not share your Novolin R FlexPen or syringes with other people, even if the needle has been changed. You may give other people a serious infection, or get a serious infection from them.

What is Novolin R?

Novolin R is a man-made insulin that is used to control high blood sugar in adults and children with diabetes mellitus.

Who should not use Novolin R?

Do not use Novolin R if you:

- are having an episode of low blood sugar (hypoglycemia).
- have an allergy to human insulin or any of the ingredients in Novolin R. See the end of this Patient Information leaflet for a complete list of ingredients in Novolin R.

Before using Novolin R, tell your healthcare provider about all of your medical conditions, including if you:

- have liver or kidney problems.
- take other medicines, especially ones called TZDs (thiazolidinediones).
- have heart failure or other heart problems. If you have heart failure, it may get worse while you take TZDs with Novolin R.
- are pregnant or plan to become pregnant. Talk with your healthcare provider about the best way to control your blood sugar if you plan to become pregnant or while you are pregnant.
- are breastfeeding or plan to breastfeed. Novolin R may pass into your breast milk. Talk with your healthcare provider about the best way to feed your baby while using Novolin R.

Tell your healthcare provider about all of the medicines you take, including prescription and over-the-counter medicines, vitamins and herbal supplements.

Before you start using Novolin R, talk to your healthcare provider about low blood sugar and how to manage it.

How should I use Novolin R?

- Read the detailed Instructions for Use that comes with your Novolin R.
- Use Novolin R exactly as your healthcare provider tells you to. Your healthcare provider should tell you how much Novolin R to use and when to use it.
- Use Novolin R about 30 minutes before eating a meal.
- Know the type, strength, and amount of insulin you use. Do not change the type or amount of insulin you use unless your healthcare provider tells you to. The amount of insulin and the best time for you to take your insulin may need to change if you use different types of insulin.
- Check your insulin label each time you give your injection to make sure you are using the correct insulin.
- Inject Novolin R under the skin (subcutaneously) of your stomach area, buttocks, upper legs (thighs), or upper arms. Do not inject Novolin R into your vein (intravenously) or use in an insulin infusion pump. Novolin R may be given into your vein only by your healthcare provider.
- Do not mix Novolin R with any other insulin except Novolin N. If Novolin R is mixed with Novolin N, Novolin R should be drawn into the syringe first. Inject immediately after mixing.
- Change (rotate) your injection sites within the area you choose with each dose to reduce your risk of getting lipodystrophy (pits in skin or thickened skin) and localized cutaneous amyloidosis (skin with lumps) at the injection sites.
- Do not use the exact same spot for each injection.
- Do not inject where the skin has pits, is thickened, or has lumps.
- Do not inject where the skin is tender, bruised, scaly or hard, or into scars or damaged skin.
- Check your blood sugar levels. Ask your healthcare provider what your blood sugars should be and when you should check your blood sugar levels.

Keep Novolin R and all medicines out of the reach of children.

Your dose of Novolin R may need to change because of:

- change in level of physical activity or exercise, weight gain or loss, increased stress, illness, change in diet, or because of other medicines you take.

What should I avoid while using Novolin R?

While using Novolin R do not:

- drive or operate heavy machinery until you know how Novolin R affects you.
- drink alcohol or use prescription or over-the-counter medicines that contain alcohol.

What are the possible side effects of Novolin R?

Novolin R may cause serious side effects that can lead to death, including:

- low blood sugar (hypoglycemia). Signs and symptoms of low blood sugar may include:
- dizziness or lightheadedness, sweating, confusion, headache, blurred vision, slurred speech, shakiness, fast heartbeat, anxiety, irritability or mood changes, hunger.
- Your healthcare provider may prescribe a glucagon emergency kit so that others can give you an injection if your blood sugar becomes too low (hypoglycemia) and you are unable to take sugar by mouth.
- severe allergic reaction (whole body reaction). Get medical help right away if you have any of these signs or symptoms of a severe allergic reaction:
- a rash over your whole body, have trouble breathing, a fast heartbeat, or sweating.
- low potassium in your blood (hypokalemia).
- heart failure. Taking certain diabetes pills called thiazolidinediones or “TZDs” with Novolin R may cause heart failure in some people. This can happen even if you have never had heart failure or heart problems before. If you already have heart failure it may get worse while you take TZDs with Novolin R. Your healthcare provider should monitor you closely while you are taking TZDs with Novolin R. Tell your healthcare provider if you have any new or worse symptoms of heart failure including:
- shortness of breath, swelling of your ankles or feet, sudden weight gain.
- Treatment with TZDs and Novolin R may need to be adjusted or stopped by your healthcare provider if you have new or worse heart failure.

Get emergency medical help if you have:

- severe hypoglycemia needing hospitalization or emergency room care, and be sure to tell the hospital staff the units of Novolin R your healthcare provider has prescribed for you.
- trouble breathing, shortness of breath, fast heartbeat, swelling of your face, tongue, or throat, sweating, extreme drowsiness, dizziness, confusion.

The most common side effects of Novolin R include:

- low blood sugar (hypoglycemia), allergic reactions including reactions at your injection site, skin thickening or pits at the injection site (lipodystrophy), weight gain, and swelling (edema) in hands or feet.

These are not all of the possible side effects of Novolin R. Call your doctor for medical advice about side effects. You may report side effects to FDA at 1-800-FDA-1088.

General information about the safe and effective use of Novolin R

Medicines are sometimes prescribed for purposes other than those listed in a Patient Information leaflet. Do not use Novolin R for a condition for which it was not prescribed. Do not give Novolin R to other people, even if they have the same symptoms you have. It may harm them.

This Patient Information leaflet summarizes the most important information about Novolin R. If you would like more information, talk with your healthcare provider. You can ask your healthcare provider or pharmacist for information about Novolin R that is written for healthcare providers.

For more information about Novolin R, call 1-800-727-6500 or go to www.novonordisk-us.com.

What are the ingredients in Novolin R?

Active ingredient: insulin human

Inactive ingredients: glycerin, metacresol, zinc, Water for Injection. Hydrochloric acid and sodium hydroxide may be added.

Novolin®, FlexPen® and Novo Nordisk® are registered trademarks of Novo Nordisk A/S.

© 2022 Novo Nordisk

Manufactured by:

Novo Nordisk Inc.

800 Scudders Mill Road

Plainsboro, New Jersey 08536

U.S. License Number 1261

For information about Novolin R contact:

Novo Nordisk Inc.

800 Scudders Mill Road

Plainsboro, New Jersey 08536

1-800-727-6500 (Se habla español)

www.novonordisk-us.com

This Patient Information has been approved by the U.S. Food and Drug Administration.

Revised: 11/2022

INSTRUCTIONS FOR USE

Novolin® R

(insulin human)

injection, for subcutaneous use

10 mL multiple-dose vial (100 units/mL, U-100)

Please read the following Instructions for Use carefully before using your Novolin® R 10 mL vial and each time you get a refill. You should read the instructions in this manual even if you have used an insulin 10 mL vial before. There may be new information.

Before starting, gather all of the supplies that you will need to use for preparing and giving your insulin injection.

Never re-use syringes and needles.

How should I use the Novolin R vial?

1. Check to make sure that you have the correct type of insulin. This is especially important if you use different types of insulin.

2. Look at the vial and the insulin. The insulin should be clear and colorless. The tamper-resistant cap should be in place before the first use. If the cap had been removed before your first use of the vial, or if the insulin is cloudy, colored, or contains any particles, do not use it and call Novo Nordisk at 1-800-727-6500.

3. Wash your hands with soap and water. Clean your injection site with an alcohol swab and let the injection site dry before you inject. Talk with your healthcare provider about how to rotate injection sites and how to give an injection.

4. If you are using a new vial, pull off the tamper-resistant cap.

Wipe the rubber stopper with an alcohol swab.

5. Do not roll or shake the vial. Shaking right before the dose is drawn into the syringe may cause bubbles or foam. This can cause you to draw up the wrong dose of insulin.

6. Pull back the plunger on the syringe until the black tip reaches the marking for the number of units you will inject.

7. Push the needle through the rubber stopper of the vial.

8. Push the plunger all the way in to force air into the vial.

9. Turn the vial and syringe upside down and slowly pull the plunger back to a few units beyond the correct dose.

10. If there are any air bubbles, tap the syringe gently with your finger to raise the air bubbles to the top. Then slowly push the plunger to the marking for your correct dose. This process should move any air bubbles present in the syringe back into the vial.

11. Check to make sure you have the right dose of Novolin R in the syringe.

12. Pull the syringe out of the vial’s rubber stopper.

13. Novolin R can be injected under the skin (subcutaneously) of your stomach area, buttocks, upper legs (thighs), or upper arms. Change (rotate) your injection sites within the area you choose for each dose to reduce your risk of getting lipodystrophy (pits in skin or thickened skin) and localized cutaneous amyloidosis (skin with lumps) at the injection sites. For each injection, change (rotate) your injection site within the area of skin that you use. Do not use the same injection site for reach injection. Do not inject where the skin has pits, is thickened, or has lumps. Do not inject where the skin is tender, bruised, scaly or hard, or into scars or damaged skin. Your healthcare provider should tell you if you need to pinch the skin before and while inserting the needle. This can vary from patient to patient so it is important to ask your healthcare provider if you did not receive instructions on pinching the skin. Insert the needle into the skin. Press the plunger of the syringe to inject the insulin. When you are finished injecting the insulin, pull the needle out of your skin. You may see a drop of Novolin R at the needle tip. This is normal and has no effect on the dose you just received. If you see blood after you take the needle out of your skin, press the injection site lightly with a piece of gauze or an alcohol wipe. Do not rub the area.

14. After your injection, do not recap the needle. Place used syringes, needles and used insulin vials in a disposable puncture-resistant sharps container, or some type of hard plastic or metal container with a screw on cap such as a detergent bottle or coffee can.

15. Ask your healthcare provider about the right way to throw away used syringes and needles. There may be state or local laws about the right way to throw away used syringes and needles. Do not throw away used needles and syringes in household trash or recycle.

How should I mix Novolin R with Novolin N?

Different insulins should be mixed only under instruction from a healthcare provider. Do not mix Novolin R with any other type of insulin except Novolin N. Novolin R should be mixed with Novolin N right before use. When you are mixing Novolin R insulin with Novolin N, always draw the Novolin R (clear) insulin into the syringe first.

1. Add together the total number of units of Novolin N and Novolin R that you need to inject. Your total dose of medicine to inject will be the amount of Novolin N and Novolin R in the syringe after drawing up both insulins. For example, if you need 5 units of Novolin N and 2 units of Novolin R, the total dose of insulin in the syringe would be 7 units.

Preparing your Novolin N and Novolin R insulins for injection:

2. Roll the Novolin N vial between your hands until all of the liquid in the vial is cloudy.

3. Pull the plunger of the syringe down so that the dark end is lined up to the number of units needed for your Novolin N. This will draw into the syringe the same amount of air as the Novolin N dose needed.

4. Put the needle through the rubber stopper of the cloudy Novolin N bottle. After you inject the air into the Novolin N vial, remove the needle from the vial but do not withdraw any of the Novolin N insulin. Putting air in the bottle makes it easier to draw the insulin out of the bottle.

5. Pull the plunger of the syringe down to the number of units needed for your Novolin R insulin. After you draw the air into the syringe, inject the air into the Novolin R vial.

Drawing up and mixing your Novolin N and Novolin R insulins for injection:

6. With the needle in place, turn the clear insulin vial of Novolin R upside down and slowly pull the plunger back to a few units beyond the right dose of Novolin R. The tip of the needle must be in the Novolin R liquid to get the full dose and not an air dose.

7. Check the syringe for air bubbles. If you see air bubbles, tap the syringe gently with your finger to raise the air bubbles to the top. Then slowly push the plunger to the marking for your correct dose. This process should move any air bubbles in the syringe back into the vial.

8. After withdrawing the needle from the Novolin R vial, insert the needle into the Novolin N vial.

9. Turn the Novolin N vial upside down with the syringe and needle still in the vial. Slowly pull the plunger back to withdraw your Novolin N dose.

Remember the total dose of medicine in the syringe should be your total dose of Novolin N and Novolin R insulins. (See Step 1 under “How should I mix Novolin R with Novolin N?”)

10. Inject your insulin right away otherwise it might not work properly.

How should I store Novolin® R?

- Do not freeze Novolin R. Do not use Novolin R if it has been frozen.
- Keep Novolin R away from heat or light.
- All unopened vials:
- Store unopened Novolin R vials in the refrigerator at 36°F to 46°F (2°C to 8°C).
- Unopened vials may be used until the expiration date printed on the label, if they have been stored in the refrigerator.
- Unopened vials should be thrown away after 42 days, if they are stored at room temperature up to 77°F (25°C).
- After vials have been opened:
- Opened Novolin R vials can be stored at room temperature up to 77°F (25°C). Do not refrigerate.
- Throw away all opened Novolin R vials after 42 days, even if they still have insulin left in them.

This Patient Instructions for Use has been approved by the Food and Drug Administration.

Manufactured by:

Novo Nordisk Inc.

800 Scudders Mill Road

Plainsboro, New Jersey 08536

1-800-727-6500

U.S. License Number 1261

Revised: 11/2022

INSTRUCTIONS FOR USE

Novolin® R FlexPen®

(insulin human)

injection, for subcutaneous use

Introduction

Please read the following instructions carefully before using your Novolin R FlexPen.

Do not share your Novolin R FlexPen with other people, even if the needle has been changed. You may give other people a serious infection, or get a serious infection from them.

Novolin R FlexPen is a disposable, single-patient-use, dial-a-dose insulin pen. You can select doses from 1 to 60 units in increments of 1 unit. Novolin R FlexPen is designed to be used with NovoFine, NovoFine Plus or NovoTwist needles.

People who are blind or have vision problems should not use Novolin R FlexPen without help from a person trained to use Novolin R FlexPen.

Getting ready

Make sure you have the following items:

- Novolin R FlexPen
- New NovoFine, NovoFine Plus or NovoTwist needle
- Alcohol swab
- Gauze pad

Preparing your Novolin R FlexPen

Wash your hands with soap and water. Before you start to prepare your injection, check the label to make sure that you are taking the right type of insulin. This is especially important if you take more than 1 type of insulin. Novolin R should look clear and colorless. Do not use your Novolin R FlexPen if the liquid contains particles or is colored.

A. Pull off the pen cap (see diagram A).

Wipe the rubber stopper with an alcohol swab.

Attaching the needle

B. Remove the protective tab from a disposable needle.

Screw the needle tightly onto your Novolin R FlexPen. It is important that the needle is put on straight (see diagram B).

Never place a disposable needle on your Novolin R FlexPen until you are ready to take your injection.

C. Pull off the big outer needle cap (see diagram C).

D. Pull off the inner needle cap and dispose of it (see diagram D).

Always use a new needle for each injection to help ensure sterility and prevent blocked needles. Do not reuse or share your needles with other people. You may give other people a serious infection, or get a serious infection from them.

Be careful not to bend or damage the needle before use.

To reduce the risk of unexpected needle sticks, never put the inner needle cap back on the needle.

Giving the airshot before each injection

Before each injection small amounts of air may collect in the cartridge during normal use. To avoid injecting air and to make sure you take the right dose of insulin:

E. Turn the dose selector to select 2 units (see diagram E).

F. Hold your Novolin R FlexPen with the needle pointing up. Tap the cartridge gently with your finger a few times to make any air bubbles collect at the top of the cartridge (see diagram F).

G. Keep the needle pointing upwards, press the push-button all the way in (see diagram G). The dose selector returns to 0.

A drop of insulin should appear at the needle tip. If not, change the needle and repeat the procedure no more than 6 times.
If you do not see a drop of insulin after 6 times, do not use the Novolin R FlexPen and contact Novo Nordisk at 1-800-727-6500.
A small air bubble may remain at the needle tip, but it will not be injected.

Selecting your dose

Check and make sure that the dose selector is set at 0.

H. Turn the dose selector to the number of units you need to inject. The pointer should line up with your dose.

The dose can be corrected either up or down by turning the dose selector in either direction until the correct dose lines up with the pointer (see diagram H). When turning the dose selector, be careful not to press the push-button as insulin will come out.

You cannot select a dose larger than the number of units left in the cartridge.

You will hear a click for every single unit dialed. Do not set the dose by counting the number of clicks you hear.

Do not use the cartridge scale printed on the cartridge to measure your dose of insulin.

Giving the injection

Give the injection exactly as shown to you by your healthcare provider. Your healthcare provider should tell you if you need to pinch the skin before injecting. Wipe the skin with an alcohol swab and let the area dry.

Novolin R can be injected under the skin (subcutaneously) of your stomach area, buttocks, upper legs (thighs), or upper arms.

Change (rotate) your injection sites within the area you choose for each dose to reduce your risk of getting lipodystrophy (pits in skin or thickened skin) and localized cutaneous amyloidosis (skin with lumps) at the injection sites. Do not use the same injection site for each injection. Do not inject where the skin has pits, is thickened, or has lumps. Do not inject where the skin is tender, bruised, scaly or hard, or into scars or damaged skin.

I. Insert the needle into your skin.

Inject the dose by pressing the push-button all the way in until the 0 lines up with the pointer (see diagram I). Be careful only to push the button when injecting.
Turning the dose selector will not inject insulin.

J. Keep the needle in the skin for at least 6 seconds, and keep the push-button pressed all the way in until the needle has been pulled out from the skin (see diagram J). This will make sure that the full dose has been given.

You may see a drop of insulin at the needle tip. This is normal and has no effect on the dose you just received. If blood appears after you take the needle out of your skin, press the injection site lightly with a gauze pad or an alcohol swab. Do not rub the area.

After the injection

Do not recap the needle. Recapping can lead to a needle stick injury. Remove the needle from the Novolin R FlexPen after each injection and dispose of it. This helps to prevent infection, leakage of insulin, and will help to make sure you inject the right dose of insulin.

If you do not have a sharps container, carefully slip the needle into the outer needle cap. Safely remove the needle and throw it away as soon as you can.

- The used Novolin R FlexPen may be thrown away in your household trash after you have removed the needle.
- Put your used needles in a FDA-cleared sharps disposal container right away after use. Do not throw away (dispose of) loose needles in your household trash.
- If you do not have a FDA-cleared sharps disposal container, you may use a household container that is:
- made of a heavy-duty plastic
- can be closed with a tight-fitting, puncture-resistant lid, without sharps being able to come out
- upright and stable during use
- leak-resistant
- properly labeled to warn of hazardous waste inside the container
- When your sharps disposal container is almost full, you will need to follow your community guidelines for the right way to dispose of your sharps disposal container. There may be state or local laws about how you should throw away used needles and syringes. For more information about safe sharps disposal, and for specific information about sharps disposal in the state that you live in, go to the FDA’s website at: http://www.fda.gov/safesharpsdisposal.
  Do not dispose of your used sharps disposal container in your household trash unless your community guidelines permit this. Do not recycle your used sharps disposal container.
- When there is not enough medicine left in your Novolin R FlexPen for your prescribed dose, the Novolin R FlexPen may be thrown away in your household trash after you have removed the needle. The Novolin R FlexPen prevents the cartridge from being completely emptied. It is designed to deliver 300 units.

K. Put the pen cap on the Novolin R FlexPen and store the Novolin R FlexPen without the needle attached (see diagram K). Storing without the needle attached helps prevent leaking, blocking of the needle, and air from entering the Pen.

How should I store Novolin R FlexPen?

- Do not freeze Novolin R. Do not use Novolin R if it has been frozen.
- Keep Novolin R away from heat and light.
- Until first use:
- Store unused Novolin R FlexPen in the refrigerator at 36°F to 46°F (2°C to 8°C).
- Unused Novolin R FlexPen may be used until the expiration date printed on the label, if kept in the refrigerator at 36°F to 46°F (2°C to 8°C).
- Unused Novolin R FlexPen stored at room temperature should be thrown away after 28 days.
- In-use:
- Store the Novolin R FlexPen you are currently using out of the refrigerator at room temperature up to 86°F (30°C) for up to 28 days.
- The Novolin R FlexPen you are using should be thrown away after 28 days, even if it still has insulin left in it.
- Store the Novolin R FlexPen without the needle attached.

Maintenance

For the safe and proper use of your Novolin R FlexPen be sure to handle it with care. Avoid dropping your Novolin R FlexPen as it may damage it. If you are concerned that your Novolin R FlexPen is damaged, use a new one. You can clean the outside of your Novolin R FlexPen by wiping it with a damp cloth. Do not soak or wash your Novolin R FlexPen as it may damage it. Do not refill your Novolin R FlexPen.

Remove the needle from Novolin R FlexPen after each injection. This helps to ensure sterility, prevent leakage of insulin, and will help to make sure you inject the right dose of insulin for future injections.

Be careful when handling used needles to avoid needle sticks and transfer of infectious diseases.

Keep your Novolin R FlexPen and needles out of the reach of children.

Use Novolin R FlexPen as directed to treat your diabetes.

Do not share your Novolin R FlexPen or needles with other people. You may give other people a serious infection, or get a serious infection from them.

Always use a new needle for each injection.

Novo Nordisk is not responsible for harm due to using this insulin pen with products not recommended by Novo Nordisk.

As a precautionary measure, always carry a spare insulin delivery device in case your Novolin R FlexPen is lost or damaged.

Remember to keep the disposable Novolin R FlexPen with you. Do not leave it in a car or other location where it can get too hot or too cold.

This Instructions for Use has been approved by the U.S. Food and Drug Administration.

Manufactured by:

Novo Nordisk Inc.

800 Scudders Mill Road

Plainsboro, New Jersey 08536

1-800-727-6500

U.S. License Number 1261

Revised: 11/2022

PRINCIPAL DISPLAY PANEL – 10 mL Vial

NDC 0169-1833-11

Novolin® R

(insulin human) injection

100 units/mL (U-100)

For subcutaneous or intravenous use

10 mL multiple-dose vial

Novo Nordisk®

Principal Display Panel – 10 mL Vial ReliOn

NDC 0169-1833-02

Novolin®R

(insulin human) injection

100 units/mL (U-100)

For subcutaneous or intravenous use

10 mL multiple-dose vial

ReliOn®

PRINCIPAL DISPLAY PANEL - 3 mL FlexPen

NDC 0169-3003-15 List 300315

Novolin®R

FlexPen®

(insulin human) injection

For Single Patient Use Only

100 units/mL (U-100)

5 x 3 mL Prefilled Pens

For subcutaneous use only

Recommended for use with NovoFine®, NovoFine®

Plus or NovoTwist® disposable needles.

Store unopened pens refrigerated at 36°F to 46°F

(2°C to 8°C) in the original carton to protect from

light until expiration date or first use.

Do not freeze. After first use, store at room

temperature (up to 86°F [30°C]), discard after 28 days.

Dispense in this sealed carton.

R

novo nordisk®

Principal Display Panel – 3 mL FlexPen ReliOn

NDC 0169-3003-25 List 300325

Novolin® R

FlexPen®

(insulin human) injection

For Single Patient Use Only

100 units/mL (U-100)

5 x 3 mL Prefilled Pens

For subcutaneous use only

Recommended for use with NovoFine®, NovoFine®

Plus or NovoTwist® disposable needles.

Store unopened pens refrigerated at 36°F to 46°F

(2°C to 8°C) in the original carton to protect from

light until expiration date or first use.

Do not freeze. After first use, store pen at

room temperature (up to 86°F [30°C]), discard

after 28 days.

Dispense in this sealed carton.

R

ReliOn®